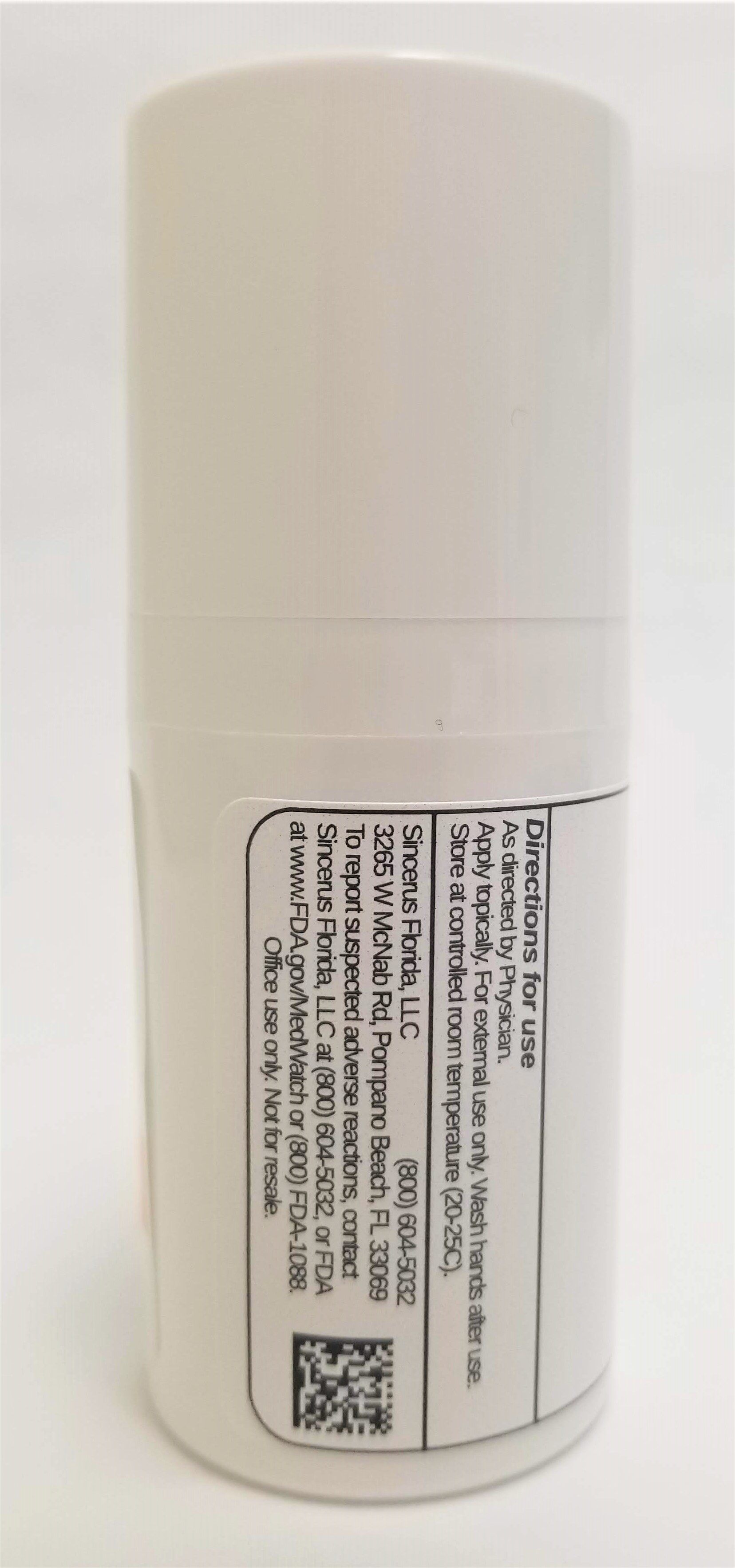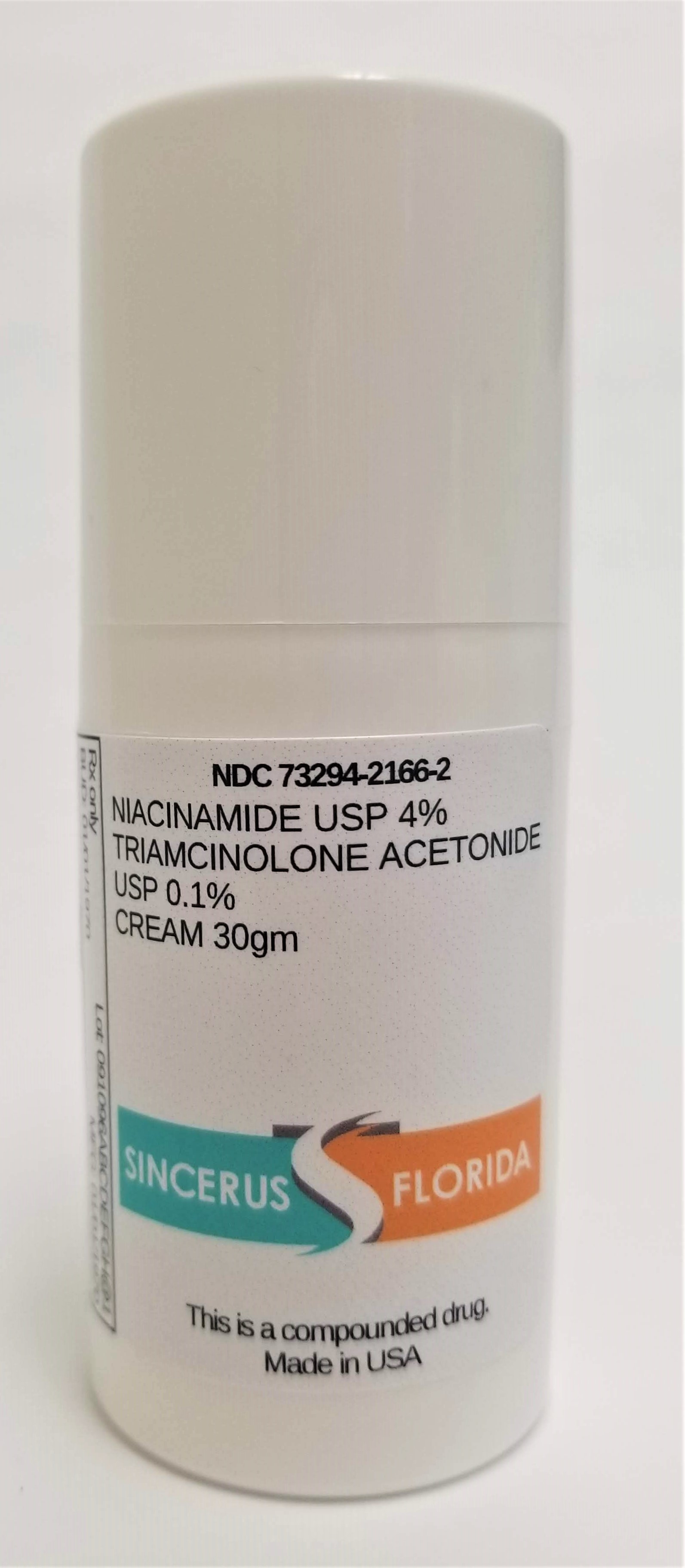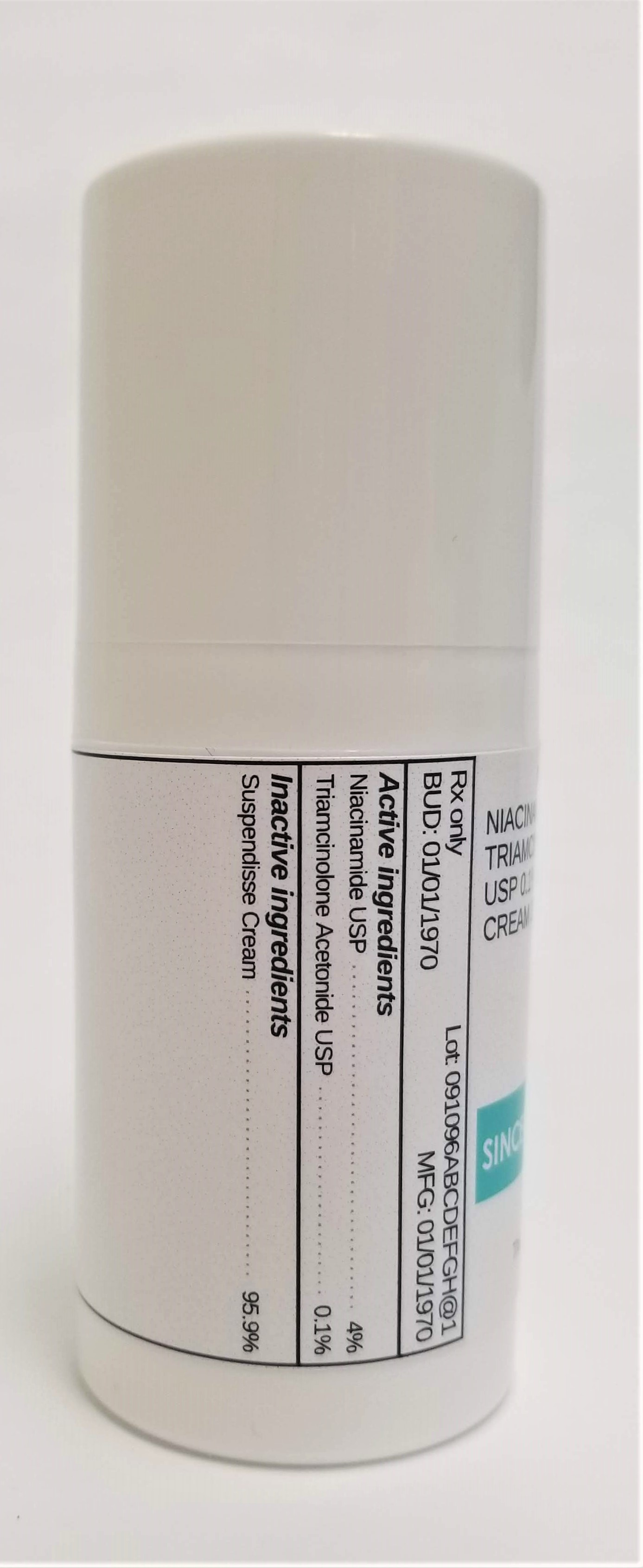 DRUG LABEL: NIACINAMIDE 4% / TRIAMCINOLONE ACETONIDE 0.1%
NDC: 72934-2166 | Form: CREAM
Manufacturer: Sincerus Florida, LLC
Category: prescription | Type: HUMAN PRESCRIPTION DRUG LABEL
Date: 20190513

ACTIVE INGREDIENTS: NIACINAMIDE 4 g/100 g; TRIAMCINOLONE ACETONIDE 0.1 g/100 g

NIACINAMIDE 4% / TRIAMCINOLONE ACETONIDE 0.1%